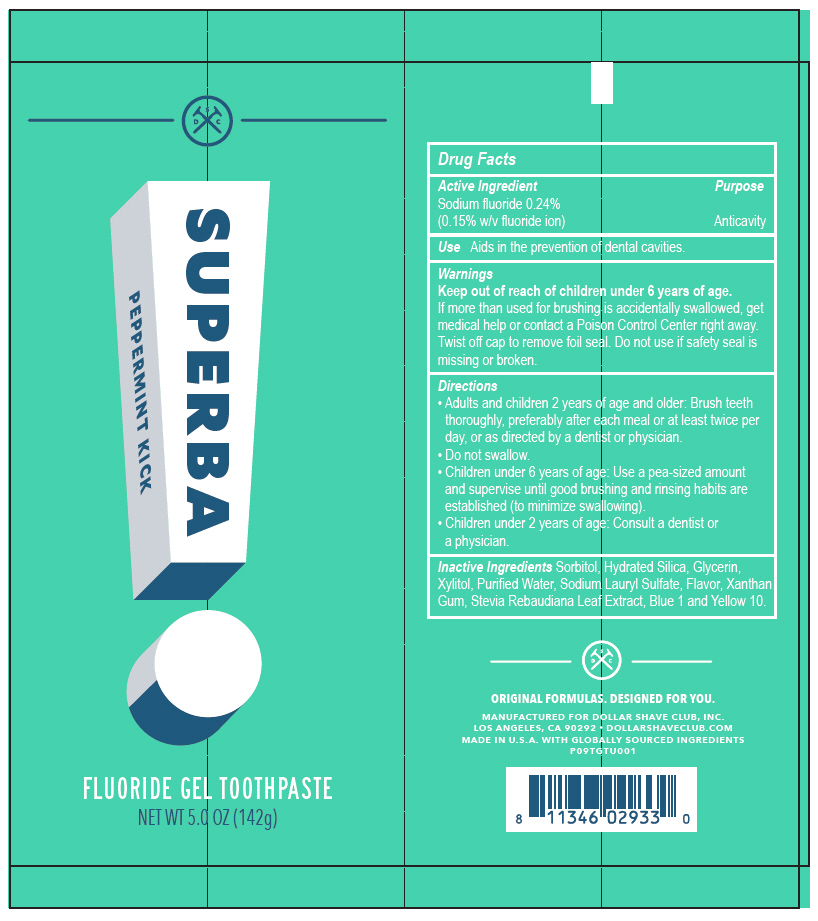 DRUG LABEL: Dollar Shave Club
NDC: 69522-1112 | Form: GEL, DENTIFRICE
Manufacturer: Dollar Shave Club
Category: otc | Type: HUMAN OTC DRUG LABEL
Date: 20180607

ACTIVE INGREDIENTS: Sodium fluoride 1.5 mg/1 g
INACTIVE INGREDIENTS: Sorbitol; Hydrated silica; WATER; Xylitol; Glycerin; Xanthan Gum; Sodium lauryl sulfate; STEVIA REBAUDIUNA LEAF; FD&C BLUE NO. 1; D&C YELLOW NO. 10

Dollar Shave Club

Drug Facts

Active Ingredient

Sodium fluoride 0.24%
(0.15% w/v fluoride ion)

Purpose

Anticavity

Use

Aids in the prevention of dental cavities.

Warnings

Keep out of reach of children under 6 years of age.

If more than used for brushing is accidentally swallowed, get medical help or contact a Poison Control Center right away.

Twist off cap to remove foil seal. Do not use if safety seal is missing or broken.

Directions

- Adults and children 2 years of age and older: Brush teeth thoroughly, preferably after each meal or at least twice per day, or as directed by a dentist or physician.
- Do not swallow.
- Children under 6 years of age: Use a pea-sized amount and supervise until good brushing and rinsing habits are established (to minimize swallowing).
- Children under 2 years of age: Consult a dentist or a physician.

Inactive Ingredients

Sorbitol, Hydrated Silica, Glycerin, Xylitol, Purified Water, Sodium Lauryl Sulfate, Flavor, Xanthan Gum, Stevia Rebaudiana Leaf Extract, Blue 1 and Yellow 10.

PRINCIPAL DISPLAY PANEL - 142 g Tube Label

SUPERBA

PEPPERMINT KICK

FLUORIDE GEL TOOTHPASTE

NET WT 5.0 OZ (142g)